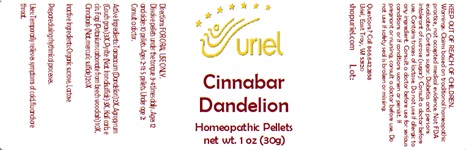 DRUG LABEL: Cinnabar Dandelion
NDC: 48951-3225 | Form: PELLET
Manufacturer: Uriel Pharmacy Inc.
Category: homeopathic | Type: HUMAN OTC DRUG LABEL
Date: 20241204

ACTIVE INGREDIENTS: CARBONATE ION 10 [hp_X]/1 1; MERCURIC CATION 20 [hp_X]/1 1; ELYMUS REPENS ROOT 3 [hp_X]/1 1; FERROUS CATION 3 [hp_X]/1 1; TARAXACUM OFFICINALE 2 [hp_X]/1 1
INACTIVE INGREDIENTS: LACTOSE, UNSPECIFIED FORM; SUCROSE

Cinnabar Dandelion

INDICATIONS AND USAGE

Directions: FOR ORAL USE ONLY.

DOSAGE AND ADMINISTRATION

Dissolve pellets under the tongue 3-4 times daily. Ages 12 and older: 10 pellets. Ages 2-11: 5 pellets. Under age 2: Consult
a doctor.

ACTIVE INGREDIENT

Active Ingredients: Taraxacum (Dandelion) 2X, Agropyrum (Couch grass) 3X, Pyrite (Nat. Iron disulfide) 3X, Kali carb. e cin. Fagi (Potassium carbonate from beech wood ash) 10X, Cinnabaris (Nat. mercuric sulfide) 20X

Inactive Ingredients: Organic sucrose, Lactose

Prepared using rhythmical processes.

PURPOSE

Uses: Temporarily relieves symptoms of cold, flu and sore throat.

KEEP OUT OF REACH OF CHILDREN.

WARNINGS

Warnings: Claims based on traditional homeopathic practice, not accepted medical evidence. Not FDA evaluated. Contains sugar. Diabetics and persons intolerant of sucrose (sugar): Consult a doctor before use. Contains traces of lactose. Do not use if allergic to any ingredient. Consult a doctor before use for serious conditions or if conditions worsen or persist. If pregnant or nursing, consult a doctor before use. Do not use if safety seal is broken or missing.

Questions? Call 866.642.2858
Made by Uriel, East Troy, WI 53120
shopuriel.com Lot: